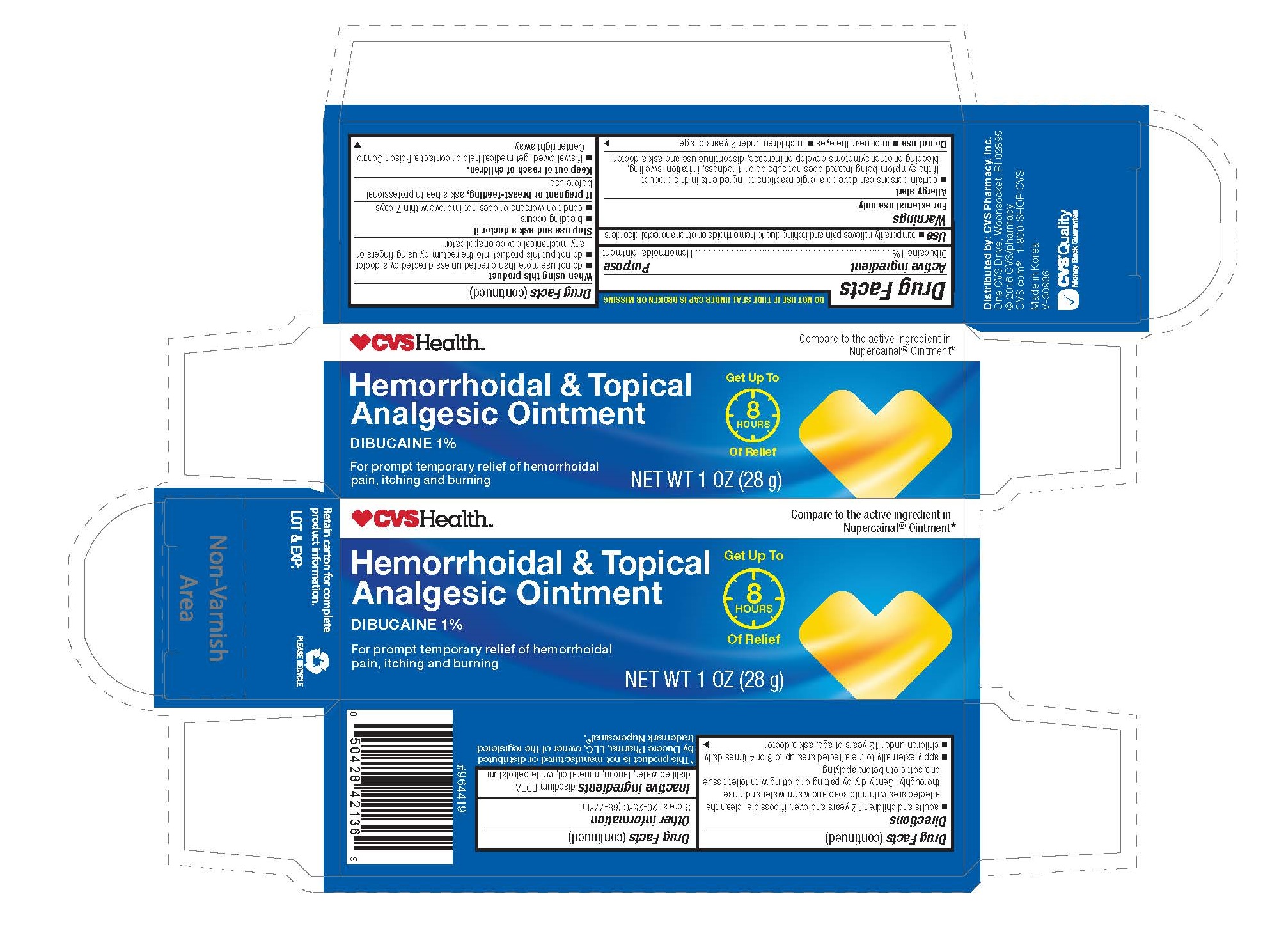 DRUG LABEL: CVS Hemorrhoidal Topical Analgesic
NDC: 59779-997 | Form: OINTMENT
Manufacturer: CVS Pharmacy, Inc.
Category: otc | Type: HUMAN OTC DRUG LABEL
Date: 20160912

ACTIVE INGREDIENTS: DIBUCAINE 10 mg/1 g
INACTIVE INGREDIENTS: DISODIUM EDTA-COPPER; WATER; LANOLIN; MINERAL OIL; PETROLATUM

Active Ingredient Purpose

Dibucaine 1%...................................... Local anesthetic

Use

temporarily relives pain and itching due to hemorrhoids or other anorectal disorders

Warnings

For external use only

Allergy Alert

- Certain persons can develop allergic reactions to ingredietns in this product. If the symptoms being treated does not subside or if redness, irritation, swelling, bleeding or other symptoms develop or increase, discontinue use and ask a doctor.

Do not use

- in or near the eyes
- in children under 2 years of age

When using this product

- do not use more than directed unless directed by a doctor
- do not put this product into the rectum by using fingers or any mechanical device or applicator

Stop use and ask a doctor if

- bleeding occurs
- condition worsens or does not improve within 7 days

PREGNANCY OR BREAST FEEDING

If pregnant or breast-feeding, ask a health professional before use.

Keep out of reach of children. If swallowed, get medical help or contact a Poison Control Center right away.

Directions

- adults and children 12 years and over: if possible, clean the affected area with mild soap and warm water and rinse thoroughly. Gently dry by patting or blotting with toilet tissue or a soft cloth before applying
- apply externally to the affected area up to 3 or 4 times daily
- children under 12 years of age: ask a doctor

Other information

store at 20-25°C (68-77°F)

Inactive ingredients

disodium EDTA, distilled water, lanolin, mineral oil, white petrolatum

DOSAGE AND ADMINISTRATION

DISTRIBUTED BY:

CVS PHARMACY, INC.

ONE CVS DRIVE

WOONSOCKET, RI 02895 USA